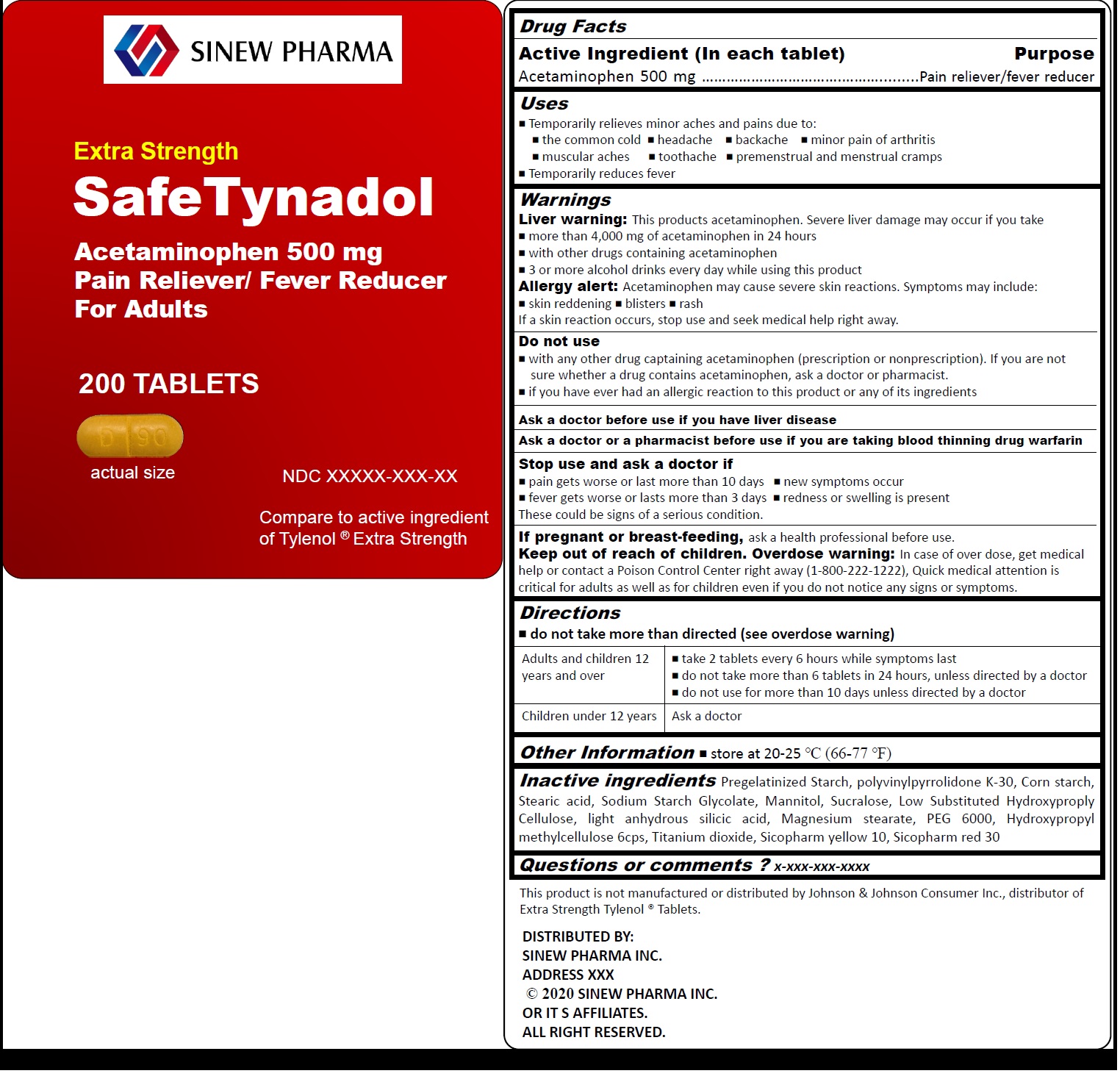 DRUG LABEL: SafeTynadol
NDC: 81389-001 | Form: TABLET, COATED
Manufacturer: Sinew Pharma Inc.
Category: otc | Type: HUMAN OTC DRUG LABEL
Date: 20231028

ACTIVE INGREDIENTS: ACETAMINOPHEN 500 mg/1 1
INACTIVE INGREDIENTS: POVIDONE K30; STARCH, CORN; STEARIC ACID; SODIUM STARCH GLYCOLATE TYPE A; MANNITOL; SUCRALOSE; LOW-SUBSTITUTED HYDROXYPROPYL CELLULOSE, UNSPECIFIED; SILICON DIOXIDE; MAGNESIUM STEARATE; POLYETHYLENE GLYCOL 6000; HYPROMELLOSE 2910 (6 MPA.S); TITANIUM DIOXIDE

SafeTynadol

ActiveIngredient(Ineachtablet)

Acetaminophen 500mg

Purpose

Pain reliever/fever reducer

Uses

￭Temporarily relieves minor aches and pains due to: ￭the common cold ￭headache ￭backache ￭minor pain of arthritis ￭muscular aches ￭toothache ￭premenstrual and menstrual cramps ￭Temporarily reduces feverr

Warnings

This products acetaminophen. Severe liver damage may occur if you take ￭more than 4,000 mg of acetaminophen in 24 hours ￭with other drugs containing acetaminophen ￭3 or more alcohol drinks every day while using this product Acetaminophen may cause severe skin reactions. Symptoms may include: ￭skin reddening ￭blisters ￭rash If a skin reaction occurs, stop use and seek medical help right away. Liver warning: Allergy alert:

Do not use

￭with any other drug captaining acetaminophen (prescription or nonprescription). If you are not sure whether a drug contains acetaminophen, ask a doctor or pharmacist. ￭if you have ever had an allergic reaction to this product or any of its ingredients

Ask a doctor before use

if you have liver disease

Ask a doctor or a pharmacist before use

if you are taking blood thinning drug warfarin

Stop use and ask a doctor if

￭pain gets worse or last more than 10 days ￭new symptoms occur ￭fever gets worse or lasts more than 3 days ￭redness or swelling is present These could be signs of a serious condition.

If pregnant or breast-feeding,

ask a health professional before use.

Keep out of reach of children. Overdose warning:

In case of over dose, get medical help or contact a Poison Control Center right away (1-800-222-1222), Quick medical attention is critical for adults as well as for children even if you do not notice any signs or symptoms.

Directions

￭do not take more than directed (see overdose warning)

Adults and children 12 years and over | ￭take 2 tablets every 6 hours while symptoms last ￭do not take more than 6 tablets in 24 hours, unless directed by a doctor ￭do not use for more than 10 days unless directed by a doctor
Children under 12 years | Ask a doctor

Other Information

Store at 20-25 °C (66-77 °F)

Inactive ingredients

Pregelatinized Starch, polyvinylpyrrolidone K-30, Corn starch, Stearic acid, Sodium Starch Glycolate, Mannitol, Sucralose, Low Substituted Hydroxyproply Cellulose, light anhydrous silicic acid, Magnesium stearate, PEG 6000, Hydroxypropyl methylcellulose 6cps, Titanium dioxide, Sicopharm yellow 10, Sicopharm red 30

Questions or comments ?

x-xxx-xxx-xxxx